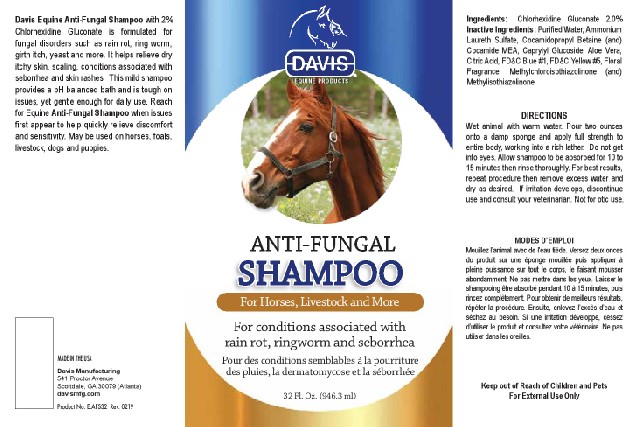 DRUG LABEL: Equine Anti-Fungal
NDC: 62570-130 | Form: SHAMPOO
Manufacturer: Davis Manufacturing and Packaging Inc
Category: animal | Type: OTC ANIMAL DRUG LABEL
Date: 20191105

ACTIVE INGREDIENTS: CHLORHEXIDINE GLUCONATE 2 g/100 g
INACTIVE INGREDIENTS: AMMONIUM LAURETH-5 SULFATE; COCAMIDOPROPYL BETAINE; COCO MONOETHANOLAMIDE; SODIUM CHLORIDE; ANHYDROUS CITRIC ACID; POLY(LAURYLGLUCOSIDE)-7; WATER; ALOE VERA LEAF; METHYLCHLOROISOTHIAZOLINONE/METHYLISOTHIAZOLINONE MIXTURE; FD&C BLUE NO. 1; FD&C YELLOW NO. 5

Davis Equine Anti-Fungal Shampoo

DESCRIPTION

Davis Equine Anti-Fungal Shampoo with 2% Chlorhexidine Gluconate is formulated for fungal disorders such as rain rot, ring worm, girth itch, yeast and more. It helps relieve dry itchy skin, scaling, conditions associated with seborrhea and skin rashes. This mild shampoo provides a pH balanced bath and is tough on issues, yet gentle enough for daily use. Reach for Equine Anti-Fungal Shampoo when issues first appear to help quickly relieve discomfort and sensitivity. May be used on horses, foals, livestock, dogs and puppies.

ACTIVE INGREDIENT

Ingredients: Chlorhexidine Gluconate 2.0%

INACTIVE INGREDIENT

Inactive Ingredients: Purified Water, Ammonium Laureth Sulfate, Cocamidopropyl Betaine (and) Cocamide MEA, Caprylyl Glucoside, Aloe Vera, Citric Acid, FD&C Blue #1, FD&C Yellow #5, Floral Fragrance, Methylchloroisothiazolinone (and) Methylisothiazolinone

INSTRUCTIONS FOR USE

DIRECTIONS Wet animal with warm water. Pour two ounces onto a damp sponge and apply full strength to entire body, working into a rich lather. Do not get into eyes. Allow shampoo to be absorbed for 10 to 15 minutes then rinse thoroughly. For best results, repeat procedure then remove excess water and dry as desired. If irritation develops, discontinue use and consult your veterinarian. Not for otic use.

French instructions

MODES D’EMPLOI Mouillez l’animal avec de l'eau tiède. Versez deux onces du produit sur une éponge mouillée puis appliquer à pleine puissance sur tout le corps, le faisant mousser abondamment. Ne pas mettre dans les yeux. Laisser le shampooing être absorbé pendant 10 à 15 minutes, puis rincez complètement. Pour obtenir de meilleurs résultats, répéter la procédure. Ensuite, enlevez l’excès d’eau et séchez au besoin. Si une irritation développe, cessez d’utiliser le produit et consultez votre vétérinaire. Ne pas utiliser dans les oreilles.

Keep out of Reach of Children and Pets For External Use Only

MADE IN THE USA

Davis Manufacturing 541 Proctor Avenue Scottdale, GA 30079 (Atlanta) davismfg.com

Product No. E.AFS32 Rev. 0219

PACKAGE LABEL

Equine Products

ANTI-FUNGAL

SHAMPOO

For Horses, Livestock and More

For conditions associated with rain rot, ringworm and seborrhea Pour des conditions semblables à la pourriture des pluies, la dermatomycose et la séborrhée